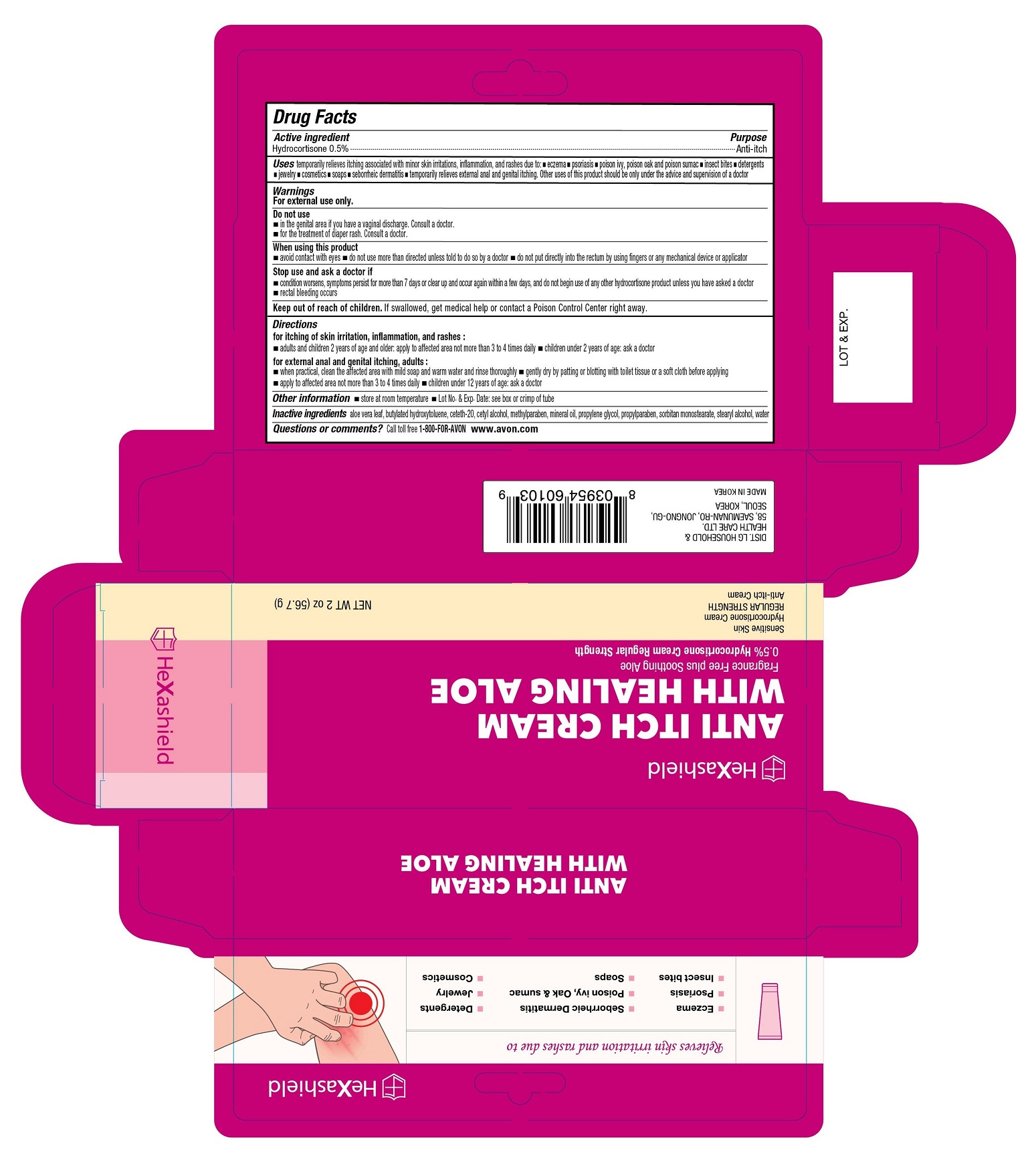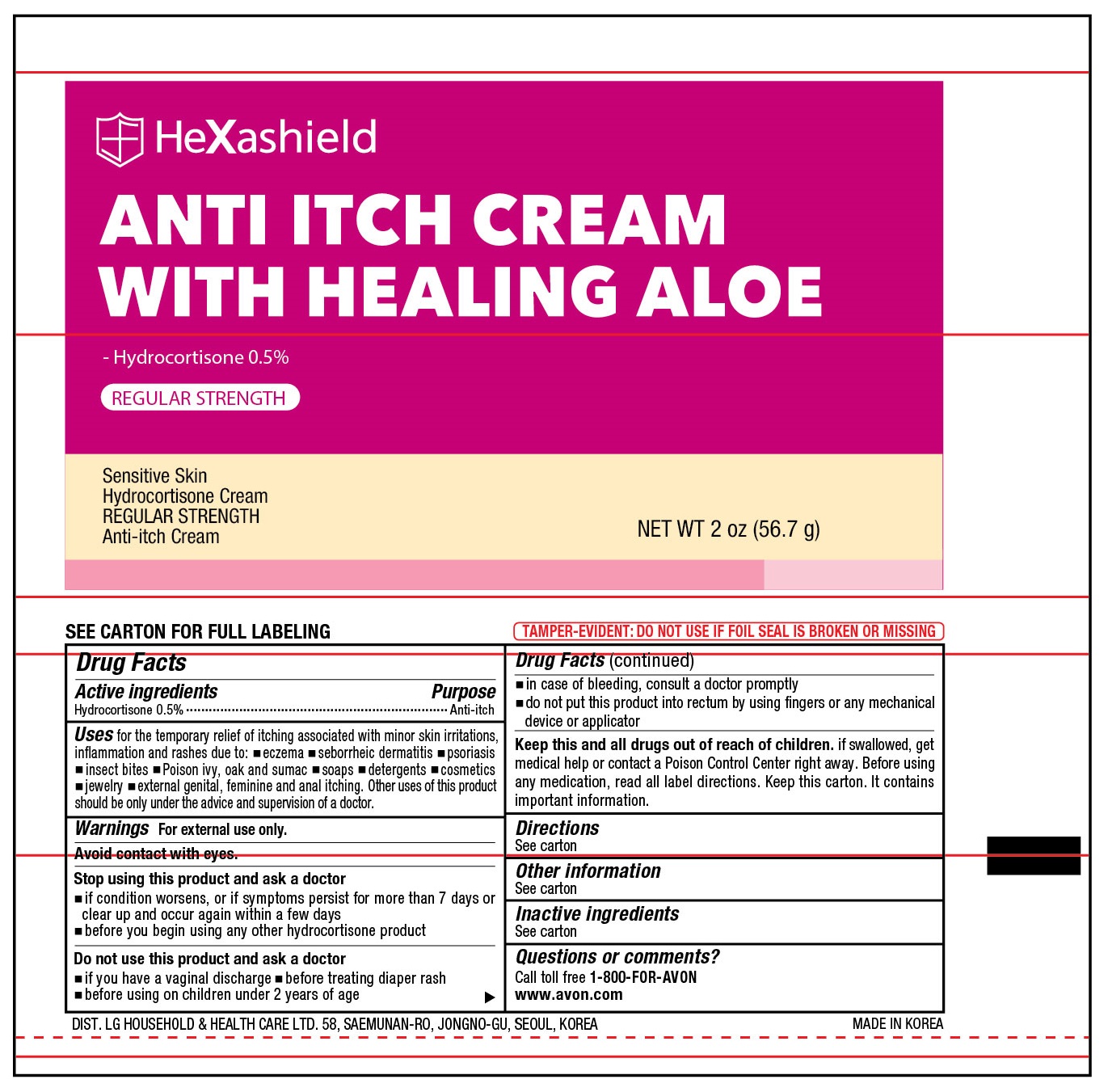 DRUG LABEL: HeXashield Anti Itch
NDC: 43136-203 | Form: CREAM
Manufacturer: Tai Guk Pharm. Co., Ltd.
Category: otc | Type: HUMAN OTC DRUG LABEL
Date: 20250101

ACTIVE INGREDIENTS: HYDROCORTISONE 5 mg/1 g
INACTIVE INGREDIENTS: STEARYL ALCOHOL; WATER; ALOE VERA LEAF; BUTYLATED HYDROXYTOLUENE; SORBITAN MONOSTEARATE; CETETH-20; CETYL ALCOHOL; MINERAL OIL; METHYLPARABEN; PROPYLENE GLYCOL; PROPYLPARABEN

HeXashield Anti Itch Cream with Healing Aloe

Active Ingredient

Hydrocortisone 0.5 %

Purpose

Anti-Itch

Uses

temporary relief of itching associated with minor skin irritations, inflammation, and rashes due to:

- eczema
- psoriasis
- poison ivy, oak or sumac
- insect bites
- detergents
- jewelry
- cosmetics
- soaps
- seborrheic dermatitis
- temporarily relieves external anal and genital itching

Other uses of this product should be only under the advice and supervision of doctor

Warnings

For external use only.

Do not use

- in the genital area if you have a vaginal discharge. Consult a doctor.
- for the treatment of diaper rash. Consult a doctor.

When using this product

- avoid contact with eyes
- do not use more than directed unless told to do so by a doctor
- do not put directly into the rectum by using fingers or any mechanical device or applicator

Stop use and ask a doctor if

- condition worsens, symptoms persist for more than 7 days or clear up and occur again within a few days, and do not begin use of any other hydrocortisone product unless you have asked a doctor
- rectal bleeding occurs

Keep out of reach of children.

If swallowed, get medical help or contact a Poison Control Center right away.

Directions

for itching of skin irritation, inflammation, and rashes :

- adults and children 2 years of age and older: apply to affected area not more than 3 to 4 times daily
- children under 2 years of age: ask a doctor

for external anal and genital itching, adults :

- when practical, clean the affected area with mild soap and warm water and rinse thoroughly
- gently dry by patting or blotting with toilet tissue or a soft cloth before applying
- apply to affected area not more than 3 to 4 times daily
- children under 12 years of age: ask a doctor

Other information

- store at room temperature
- Lot No. & Exp. Date: see box or crimp of tube

Inactive Ingredients

aloe vera leaf, butylated hydroxytolune, ceteth-20, cetyl alcohol, methylparaben, mineral oil, propylene glycol, propylparaben, sorbitan monostearate, stearyl alcohol, water

Questions or comments?

Call toll free 1-800-FOR-AVON

www.avon.com

Principal Display Panel

HeXasheild

Relieves skin irritation and rashes due to

- Eczema - Seborrheic Dermatitis - Detergents
- Psoriasis - Poison ivy, Oak & sumac - Jewelry
- Insect bites - Soaps - Cosmetics

HeXasheild

ANTI ITCH CREAM
WITH HEALING ALOE

Fragrance Free plus Soothing Aloe
0.5% Hydrocortisone Cream Regular Strength

Sensitive Skin
Hydrocortisone Cream
REGULAR STRENGTH
Anti-Itch Cream

NET WT 2 oz (57 g)

Dist. LG HOUSEHOLD & HEALTH CARE LTD.
58, SAEMUNAN-RO, JONGNO-GU, SEOUL, KOREA
MADE IN KOREA